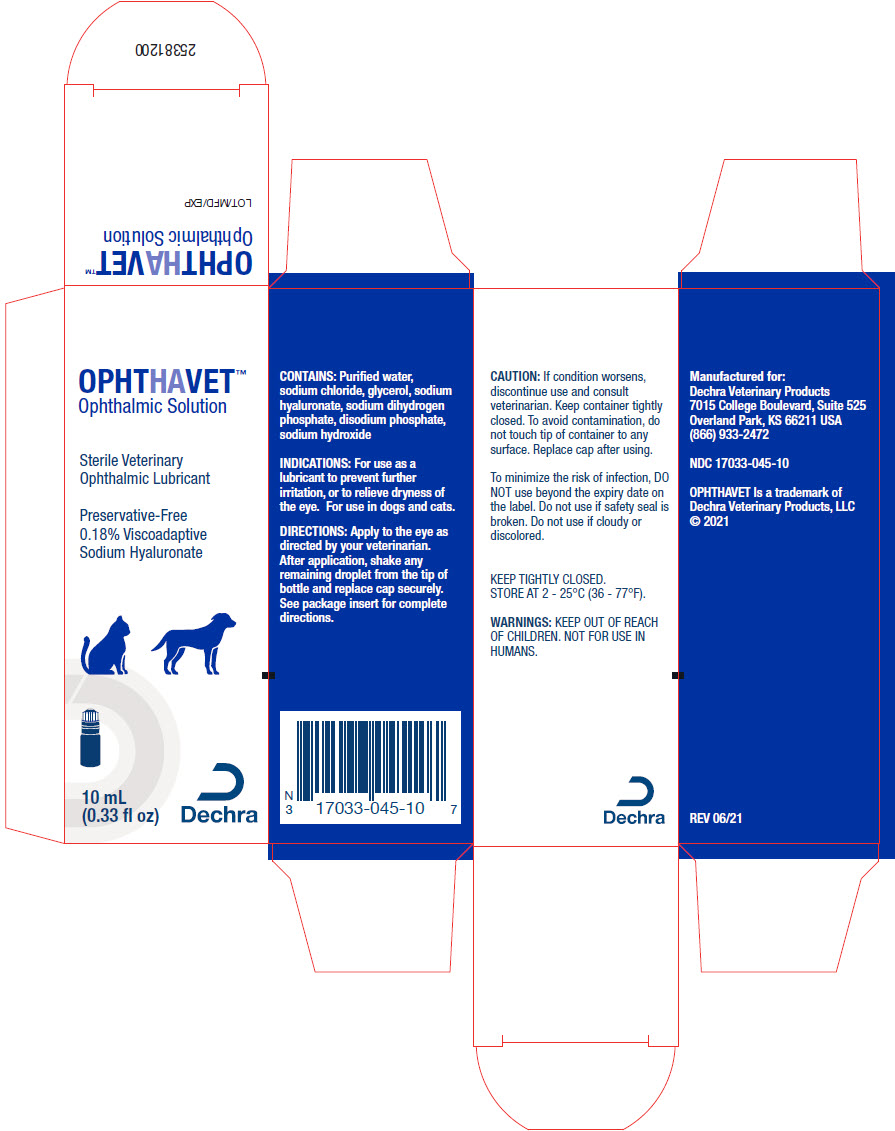 DRUG LABEL: OphtHAvet
NDC: 17033-045 | Form: SOLUTION
Manufacturer: Dechra Veterinary Products
Category: animal | Type: OTC ANIMAL DRUG LABEL
Date: 20211028

ACTIVE INGREDIENTS: HYALURONATE SODIUM 1.8 mg/1 mL

OphtHAvet™ Ophthalmic Solution

Sterile Veterinary Ophthalmic Lubricant

Preservative-Free

0.18% Viscoadaptive Sodium Hyaluronate

CONTAINS:

Purified water, sodium chloride, glycerol, sodium hyaluronate, sodium dihydrogen phosphate, disodium phosphate, sodium hydroxide

INDICATIONS:

For use as a lubricant to prevent further irritation, or to relieve dryness of the eye. For use in dogs and cats.

CAUTION:

If condition worsens, discontinue use and consult veterinarian. Keep container tightly closed. To avoid contamination, do not touch tip of container to any surface including the eye, the eyelid or your fingers. Replace cap after using. To minimize the risk of infection, DO NOT use beyond the expiry date on the label. Do not use if safety seal is broken. Do not use if cloudy or discolored.

DIRECTIONS:

Apply to the eye as directed by your veterinarian.

OPHTHAVET Ophthalmic Solution provides blink-activated lubrication and moistening for the eye surface during the day or night.

- Wash hands before use.
- Tilt the animal's head up slightly and pull the lower eyelid down to create a small area to apply the drop.
- While holding the bottle above the eye, press gently to release one drop onto the eye.
- Repeat the process in the other eye, if needed.
- After application, shake any remaining droplet from the tip of bottle and replace cap securely. This will help to prevent contamination of the bottle.
- Can be applied as often as directed by your veterinarian.
- If you are applying any other eye drops or ointments, wait at least 15 minutes between each application.

STORAGE AND HANDLING

KEEP TIGHTLY CLOSED

STORE AT 2 - 25°C (36 - 77°F).

WARNINGS

WARNING: KEEP OUT OF REACH OF CHILDREN.

NOT FOR USE IN HUMANS.

HOW SUPPLIED:

OPHTHAVET Ophthalmic Solution is supplied in a bottle with a fill volume of 10 mL (0.33 fl oz). Contents are sterile and preservative-free.

NDC: 17033-045-10

MANUFACTURED FOR:
Dechra Veterinary Products
7015 College Boulevard, Suite 525
Overland Park, KS 66211 USA
(866) 933-2472

OPHTHAVET is a trademark of
Dechra Veterinary Products, LLC
© 2021

Rev. 06/21
23382400

PRINCIPAL DISPLAY PANEL - 10 mL Bottle Carton

OPHTHAVET™
Ophthalmic Solution

Sterile Veterinary
Ophthalmic Lubricant

Preservative-Free
0.18% Viscoadaptive
Sodium Hyaluronate

10 mL
(0.33 fl oz)

Dechra